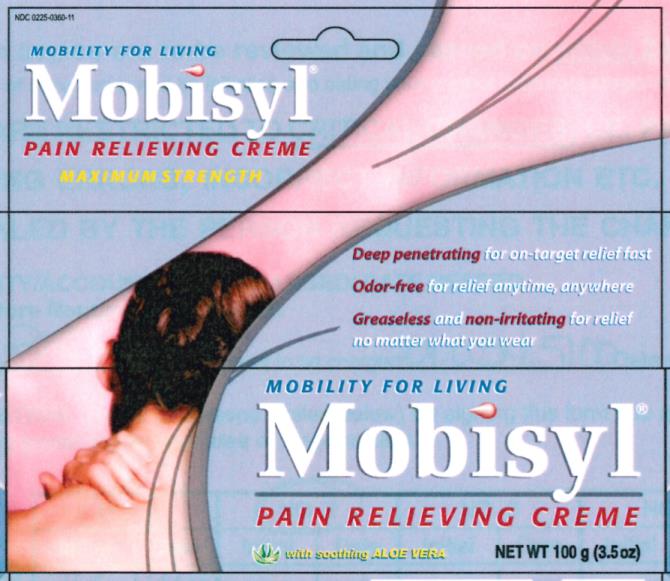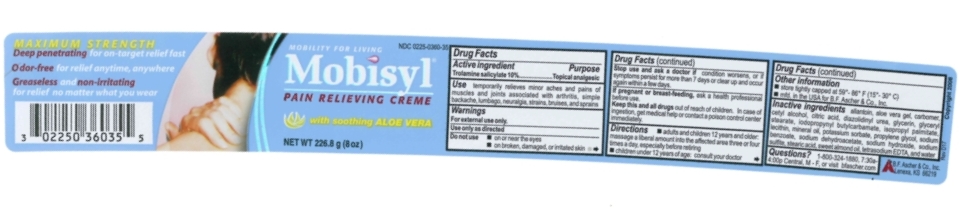 DRUG LABEL: MOBISYL
NDC: 0225-0360 | Form: CREAM
Manufacturer: BF ASCHER AND CO INC
Category: otc | Type: HUMAN OTC DRUG LABEL
Date: 20241205

ACTIVE INGREDIENTS: TROLAMINE SALICYLATE 10 g/100 g
INACTIVE INGREDIENTS: CETYL ALCOHOL; ALMOND OIL; EDETATE SODIUM; SODIUM SULFITE; ALLANTOIN; CARBOMER 940; SODIUM HYDROXIDE; IODOPROPYNYL BUTYLCARBAMATE; GLYCERIN; GLYCERYL MONOSTEARATE; MINERAL OIL; STEARIC ACID; ALOE; WATER; ISOPROPYL PALMITATE; PROPYLENE GLYCOL; ANHYDROUS CITRIC ACID; POTASSIUM SORBATE; DIAZOLIDINYL UREA; SODIUM DEHYDROACETATE; LECITHIN, SOYBEAN; SODIUM BENZOATE

Mobisyl

Active ingredient ...............................Purpose
Trolamine salicylate 10%.....................Topical analgesic

Use

For temporarily relief of minor aches and pains of muscles and joints associated with arthritis, simple backache, lumbago, neuralgia, strains, bruises, and sprains

Use

Temporarily relieves minor aches and pains of muscles and joints associated with arthritis, simple backache, lumbago, neuralgia, strains, bruises, and sprains.

Warnings
For external use only.
Use only as directed

Do not use

- on or near the eyes
- on broken, damaged, or irritated skin

Stop use and ask a doctor if condition worsens, or if symptoms persist for more than 7 days or clear up and occur again within a few days.

PREGNANCY OR BREAST FEEDING

If pregnant or breast-feeding, ask a health professional before use.

KEEP OUT OF REACH OF CHILDREN

Keep this and all drugs out of reach of children. In case of ingestion, get medical help or contact a poison control center immediately.

Directions

- adults and children 12 years and older: massage a liberal amount into the affected area three or four times a day, especially before retiring
- children under 12 years of age: consult your doctor

Other information

- store tightly capped at 59°- 86° F (15°- 30° C)
- mfd. in the USA for B.F. Ascher & Co., Inc.

INACTIVE INGREDIENT

Inactive ingredients: allantoin, aloe vera gel, carbomer, cetyl alcohol, citric acid, diazolidinyl urea, glycerin, glyceryl stearate, iodopropynyl butylcarbamate, isopropyl palmitate, lecithin, mineral oil, potassium sorbate, propylene glycol, sodium benzoate, sodium dehydroacetate, sodium hydroxide, sodium sulfite, stearic acid, sweet almond oil, tetrasodium EDTA, and water

QUESTIONS

Questions? Call 1-800-324-1880, 7:30am - 4:00pm Central, M - F, or visit www.bfascher.com

PACKAGE LABEL

Mobisyl 8oz PDP

Mobisyl 3.5oz PDP